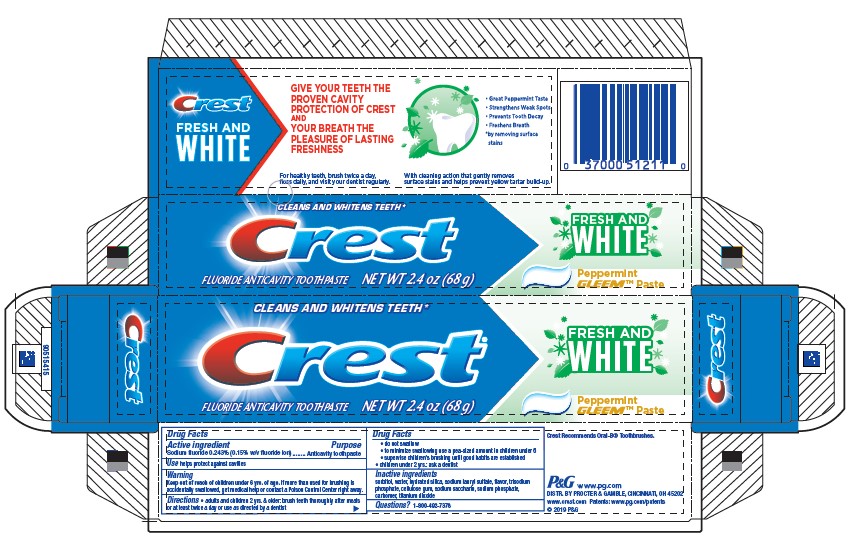 DRUG LABEL: Crest
NDC: 37000-868 | Form: PASTE, DENTIFRICE
Manufacturer: The Procter & Gamble Manufacturing Company
Category: otc | Type: HUMAN OTC DRUG LABEL
Date: 20260212

ACTIVE INGREDIENTS: SODIUM FLUORIDE 1.5 mg/1 g
INACTIVE INGREDIENTS: WATER; HYDRATED SILICA; SODIUM LAURYL SULFATE; SODIUM PHOSPHATE; CARBOXYMETHYLCELLULOSE SODIUM, UNSPECIFIED FORM; SACCHARIN SODIUM; TITANIUM DIOXIDE; SORBITOL

Crest Fresh and White Peppermint Gleem Paste

Drug Facts

Active ingredient

Sodium fluoride 0.243% (0.15% w/v fluoride ion)

Purpose

Anticavity toothpaste

Use

helps protect against cavities

Warning

Keep out of reach of children under 6 yrs. of age. If more than used for brushing is accidentally swallowed, get medical help or contact a Poison Control Center right away.

Directions

- adults and children 2 yrs. & older: brush teeth thoroughly after meals or at least twice a day or use as directed by a dentist
  - do not swallow
  - to minimize swallowing use a pea-sized amount in children under 6
  - supervise children's brushing until good habits are established
- children under 2 yrs.: ask a dentist

Inactive ingredients

sorbitol, water, hydrated silica, sodium lauryl sulfate, flavor, trisodium phosphate, cellulose gum, sodium saccharin, sodium phosphate, carbomer, titanium dioxide

Questions?

1-800-492-7378

DISTR. BY
PROCTER & GAMBLE,
CINCINNATI, OH 45202

PRINCIPAL DISPLAY PANEL - 68 g Tube Carton

CLEANS & WHITENS TEETH*

Crest®

FLUORIDE ANTICAVITY TOOTHPASTE

NET WT 2.4 OZ (68 g)

FRESH AND
WHITE

Peppermint
GLEEM™ Paste